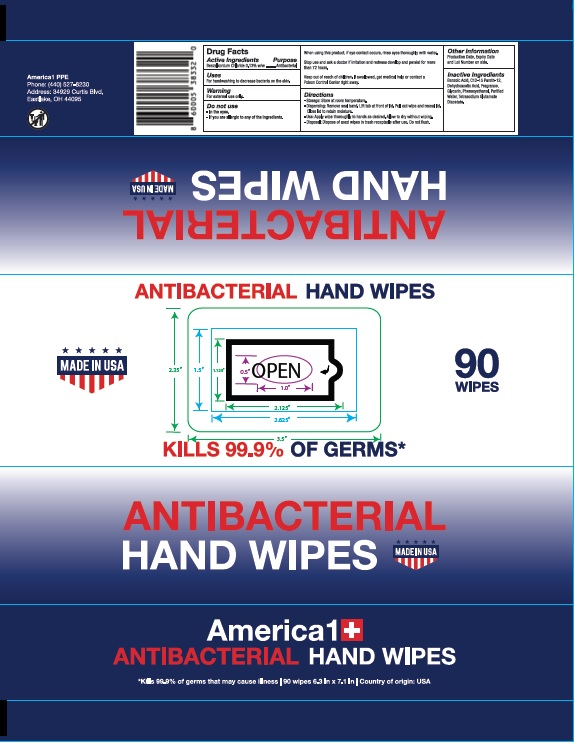 DRUG LABEL: America1  Hand Wipes
NDC: 82055-013 | Form: CLOTH
Manufacturer: America1ppe LLC
Category: otc | Type: HUMAN OTC DRUG LABEL
Date: 20210629

ACTIVE INGREDIENTS: BENZALKONIUM CHLORIDE 0.13 1/1 1
INACTIVE INGREDIENTS: BENZOIC ACID; DEHYDROACETIC ACID; C12-15 PARETH-12; GLYCERIN; PHENOXYETHANOL; WATER; TETRASODIUM GLUTAMATE DIACETATE

Antibacterial Hand Wipes

Active ingredient

Benzalkonium Chloride 0.13% w/w

Purpose

Antibacterial

Uses

For handwashing to decrease bacteria on the skin

Warning

For external use only

Do not use

- In the eyes
- If you are allergic to any of the ingredients

When using this product

if eye contact occurs, rinse eyes thoroughly with water.

Stop use and ask a doctor

if irritation and redness develops and persists for more than 72 hours

Keep out of reach of children

If swallowed, get medical help or contact a Posion Control Center right away.

Directions

- Storage: Store at room temperature
- Dispensing: Remove seal band. Lift tab at front of lid. Pull out wipe and reseal lid. Close lid to retain moisture
- Use: Apply wipe thoroughly to hands as desired. Allow to dry without wiping.
- Disposal: Dispose of used wipes in trash receptacle after use. Do not flush

Other information

Production Date, Expiry Date and Lot Number on side

Inactive ingredients

Benzoic Acid, C12-15 Pareth-12, Dehydroacetic acid, Fragrance, Glycerin, Phenoxyethanol, Purified Water, Tetrasodium Glutamate Diacetate

Principal Display Panel

NDC: 82055-013-90

America1 + ANTIBACTERIAL HAND WIPES

MADE IN USA

KILLS 99.99% OF GERMS*

* Kills 99.9% of germs that may cause illness| 90 wipes. 6.3 in X 7.1 in | Country of Origin: USA